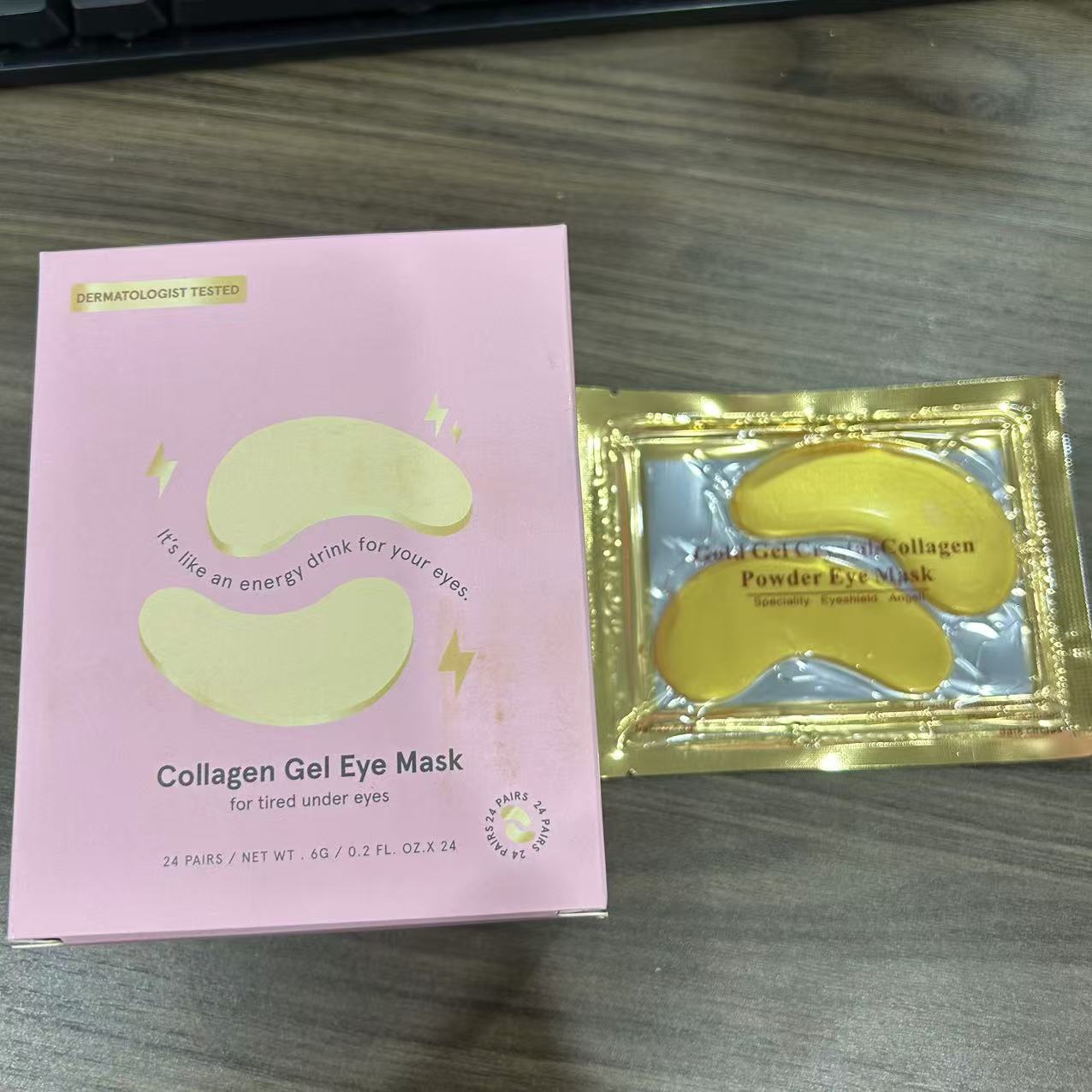 DRUG LABEL: COLLAGEN EYE MASK
NDC: 84766-0006 | Form: GEL
Manufacturer: COMFMET LIMITED
Category: otc | Type: HUMAN OTC DRUG LABEL
Date: 20241023

ACTIVE INGREDIENTS: HUMAN TYPE V COLLAGEN 0.15 g/100 g; GLUCOMANNAN 0.2 g/100 g; GLYCERIN 8.24 g/100 g
INACTIVE INGREDIENTS: TITANIUM DIOXIDE; AQUA; POTASSIUM CHLORIDE; .MU.-METHYLENE-.MU.-CHLOROBIS(.ETA.5-2,4-CYCLOPENTADIEN-1-YL)(DIMETHYLALUMINUM)TITANIUM; MICA; IRON OXIDES

ACTIVE INGREDIENT

Glycerin......8.24%
Glucomannan......0.20%
Collagen......0.15%

PURPOSE

Revitalize your under eye skin gold-infused Gold collagen Eye Mask that are remarkably refreshing and smoothing. Our gold eye masks gel pads are ultra gentle, safe, and dependable.

INDICATIONS AND USAGE

1 .After washing your face, first use makeup water to soothe your skin.

2. Take out a piece of eye film and apply it around the eyes.

3. The effect of lying flat application is better. lt can be applied for 15-20 minutes.

4. After applying, take off the eye mask and gently massage until it is absorbed

WARNINGS

For external use only.

Do not use on damaged or broken skin.

When using this product keep out of eyes. Rinse with water to remove.

Stop use and ask a doctor if rash occurs.

ASK DOCTOR

If skin rash occurs during or after use

Keep out of reach of children. If swallowed, get medical help or contact a Poison Control Center right away.

INACTIVE INGREDIENT

Aqua

Cl 77891

Cl 77019
Potassium chloride

Chondrus

Cl 77491

QUESTIONS

Email:commet515@gmail.com

DOSAGE AND ADMINISTRATION

1 .After washing your face, first use makeup water to soothe your skin.

2. Take out a piece of eye film and apply it around the eyes.

3. The effect of lying flat application is better. lt can be applied for 15-20 minutes.

4. After applying, take off the eye mask and gently massage until it is absorbed

One patch for each eye at a time.